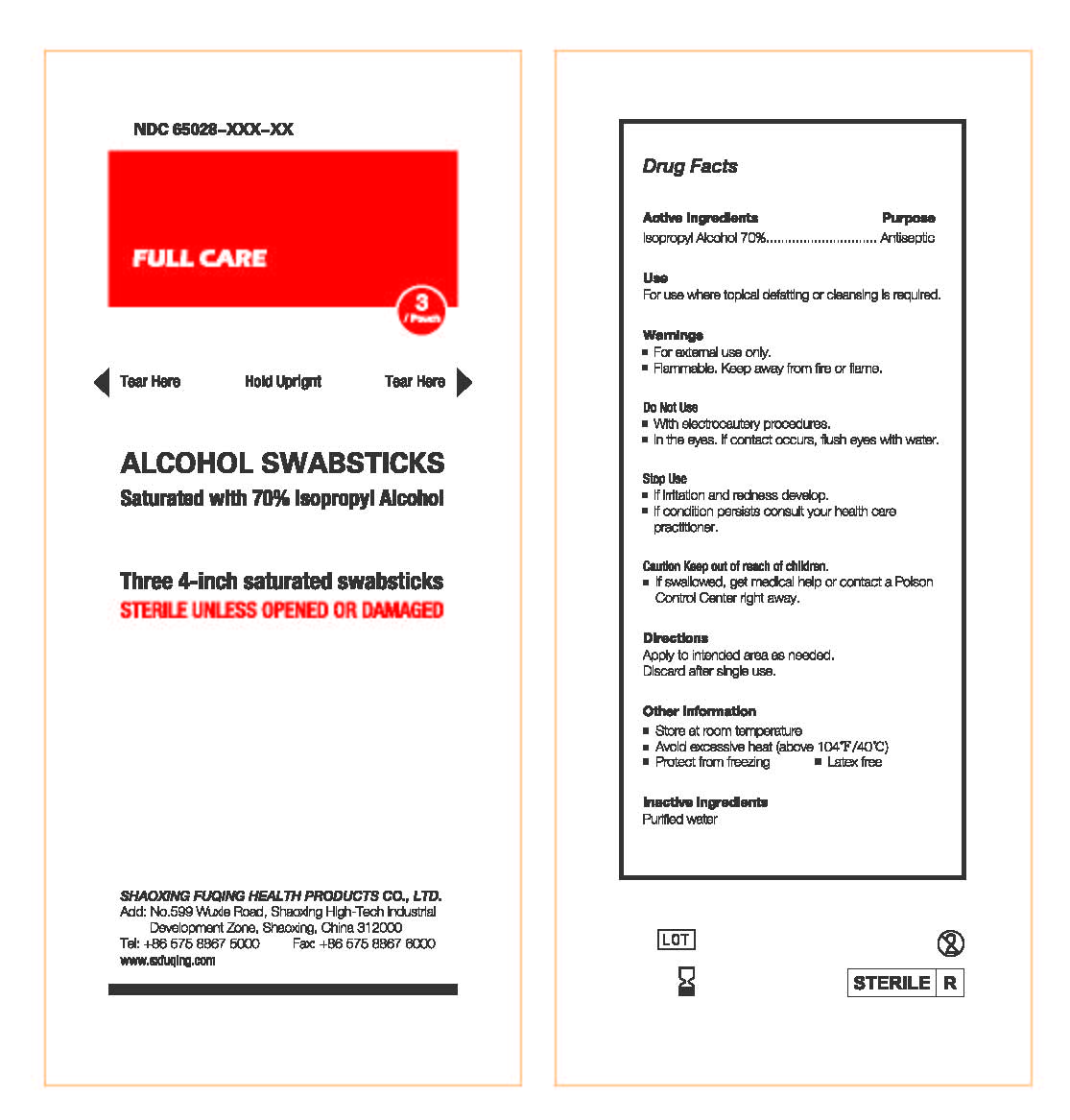 DRUG LABEL: Full Care  Alcohol Swabsticks
NDC: 65028-003 | Form: SOLUTION
Manufacturer: Shaoxing Fuqing Health Products Co., Ltd.
Category: otc | Type: HUMAN OTC DRUG LABEL
Date: 20140918

ACTIVE INGREDIENTS: ISOPROPYL ALCOHOL 1.4 g/2 mL
INACTIVE INGREDIENTS: WATER

Active Ingredient: Isopropyl Alcohol (70%)

Purpose: Antiseptic

Use:

For use where topical defatting or cleasing is required.

Warnings:

For external use only

Flammable. Keep away from fire or flame

Do not use:

With electrocautery procedures

In the eyes. If contact occurs, flush eyes with water.

Stop use:

If irritation or redness develop

If condition persists consult your healthcare practitioner

KEEP OUT OF REACH OF CHILDREN

Caution Keep out of reach of children. If swallowed, get medical help or contact a poison control center right away

Directions:

Apply to intended area as needed.

Discard after single use.

Other Information:

- Store at room temperature
- Avoid excessive heat (above 104F or 40C)
- Protect from freezing
- Latex free

Inactive Ingredient

Purified water